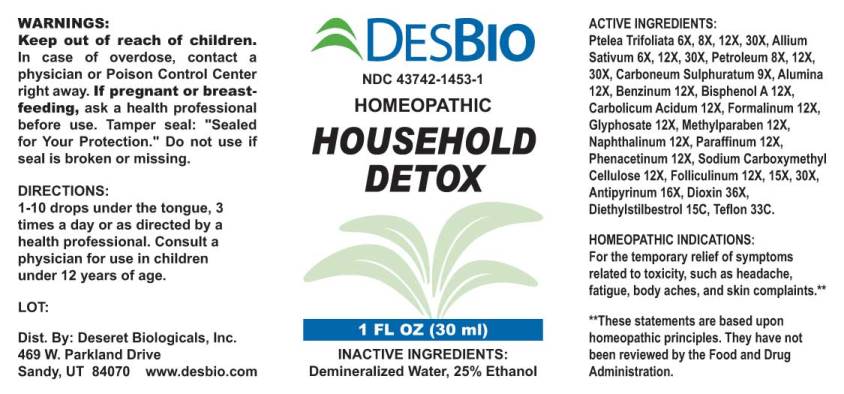 DRUG LABEL: Household Detox
NDC: 43742-1453 | Form: LIQUID
Manufacturer: Deseret Biologicals, Inc.
Category: homeopathic | Type: HUMAN OTC DRUG LABEL
Date: 20240927

ACTIVE INGREDIENTS: PTELEA TRIFOLIATA BARK 6 [hp_X]/1 mL; GARLIC 6 [hp_X]/1 mL; KEROSENE 8 [hp_X]/1 mL; CARBON DISULFIDE 9 [hp_X]/1 mL; ALUMINUM OXIDE 12 [hp_X]/1 mL; BENZENE 12 [hp_X]/1 mL; BISPHENOL A 12 [hp_X]/1 mL; PHENOL 12 [hp_X]/1 mL; FORMALDEHYDE 12 [hp_X]/1 mL; GLYPHOSATE 12 [hp_X]/1 mL; METHYLPARABEN 12 [hp_X]/1 mL; NAPHTHALENE 12 [hp_X]/1 mL; PARAFFIN 12 [hp_X]/1 mL; PHENACETIN 12 [hp_X]/1 mL; CARBOXYMETHYLCELLULOSE SODIUM, UNSPECIFIED FORM 12 [hp_X]/1 mL; ESTRONE 12 [hp_X]/1 mL; ANTIPYRINE 16 [hp_X]/1 mL; 2,3,7,8-TETRACHLORODIBENZO-P-DIOXIN 36 [hp_X]/1 mL; DIETHYLSTILBESTROL 15 [hp_C]/1 mL; POLYTETRAFLUOROETHYLENE 33 [hp_C]/1 mL
INACTIVE INGREDIENTS: WATER; ALCOHOL

Drug Facts:

ACTIVE INGREDIENTS:

Ptelea Trifoliata 6X, 8X, 12X, 30X, Allium Sativum 6X, 8X, 30X, Petroleum 8X, 12X, 30X, Carboneum Sulphuratum 9X, Alumina 12X, Benzinum 12X, Bisphenol A 12X, Carbolicum Acidum 12X, Formalinum 12X, Glyphosate 12X, Methylparaben 12X, Naphthalinum 12X, Paraffinum 12X, Phenacetinum 12X, Sodium Carboxymethyl Cellulose 12X, Folliculinum 12X, 15X, 30X, Antipyrinum 16X, Dioxin 36X, Diethylstilbestrol 15C, Teflon 33C.

HOMEOPATHIC INDICATIONS:

For the temporary relief of symptoms related to toxicity, such as headache, fatigue, body aches, and skin complaints.**

**These statements are based upon traditional homeopathic principles. They have not been reviewed by the Food and Drug Administration.

WARNINGS:

Keep out of reach of children. In case of overdose, contact physician or a Poison Control Center right away.

If pregnant or breast-feeding, ask a health professional before use.

Tamper seal: "Sealed for Your Protection." Do not use if seal is broken or missing.

Keep out of reach of children. In case of overdose, contact physician or a Poison Control Center right away.

DIRECTIONS:

1-10 drops under the tongue, 3 times a day or as directed by a health professional. Consult a physician for use in children under 12 years of age.

HOMEOPATHIC INDICATIONS:

For the temporary relief of symptoms related to toxicity, such as headache, fatigue, body aches, and skin complaints.**

**These statements are based upon traditional homeopathic principles. They have not been reviewed by the Food and Drug Administration.

INACTIVE INGREDIENTS:

Demineralized Water, 25% Ethanol

QUESTIONS:

Dist. By: Deseret Biologicals, Inc.
469 W. Parkland Drive
Sandy, UT 84070 www.desbio.com

PACKAGE LABEL DISPLAY:

DESBIO

NDC 43742-1453-1

HOMEOPATHIC

HOUSEHOLD

DETOX

1 FL OZ (30 ml)